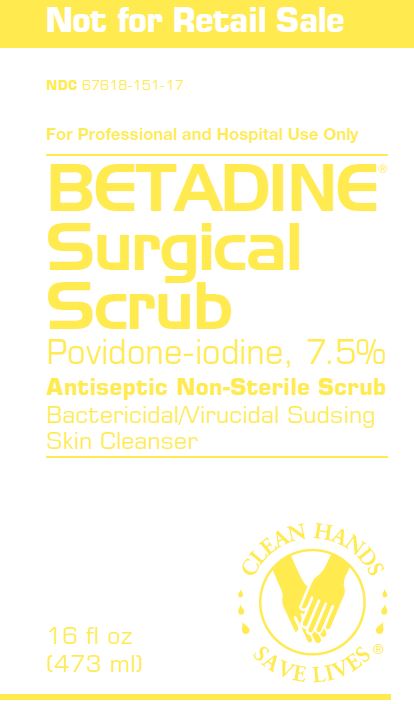 DRUG LABEL: Betadine
NDC: 67618-151 | Form: SOLUTION
Manufacturer: Atlantis Consumer Healthcare, Inc.
Category: otc | Type: HUMAN OTC DRUG LABEL
Date: 20250106

ACTIVE INGREDIENTS: POVIDONE-IODINE .075 mg/1 mL
INACTIVE INGREDIENTS: AMMONIUM NONOXYNOL-4 SULFATE; NONOXYNOL-9; WATER; SODIUM HYDROXIDE

Betadine Surgical Scrub

Drug Facts

Active ingredient

Povidone-iodine, 7.5%(0.75% available iodine)

Purpose

Antiseptic

Uses

- helps to reduce bacteria that potentially can cause skininfection
- for handwashing to reduce bacteria on the skin
- significantly reduces the number of microorganisms on thehands and forearms prior to surgery or patient care

Warnings

For external use only

Do not use this product

- in the eyes

When using this product

- prolonged exposure to wet solution may cause irritation or, rarely, severe skin reactions

Stop use and ask a doctor

- if irritation and redness develop
- in rare instances of local irritation or sensitivity

Keep out of reach of children. If swallowed, get medical help or contact a Poison Control Center right away.

Directions

1. Surgical hand scrub:
  - wet hands with water
  - spread about 5 cc (1 teaspoonful) of Scrub over both handsand forearms
  - without adding more water, scrub thoroughly for 2 1/2 to3 minutes
  - use a sponge if desired. Clean thoroughly under fingernails.
  - add a little water and develop copious suds. Rinse thoroughlyunder running water.
  - repeat the entire procedure using another 5 cc of Scrub
2. Antiseptic hand wash:
  - wet hands with water and pour about 5 cc of Scrub on hands
  - rub hands vigorously together for at least 15 seconds, coveringall surfaces
  - rinse and dry with a disposable towel

Other information

- store at 25°C (77°F); excursions permitted between 15°-30°C(59°-86°F)
- store in original container

Inactive ingredients

ammonium nonoxynol-4sulfate, nonoxynol-9, purified water, sodium hydroxide

Dist. by:
AvrioHealth L.P. Stamford, CT 06901-3431

304954-0A

PACKAGE LABEL

Betadine Surgical Scrub
NDC 67618-151-17